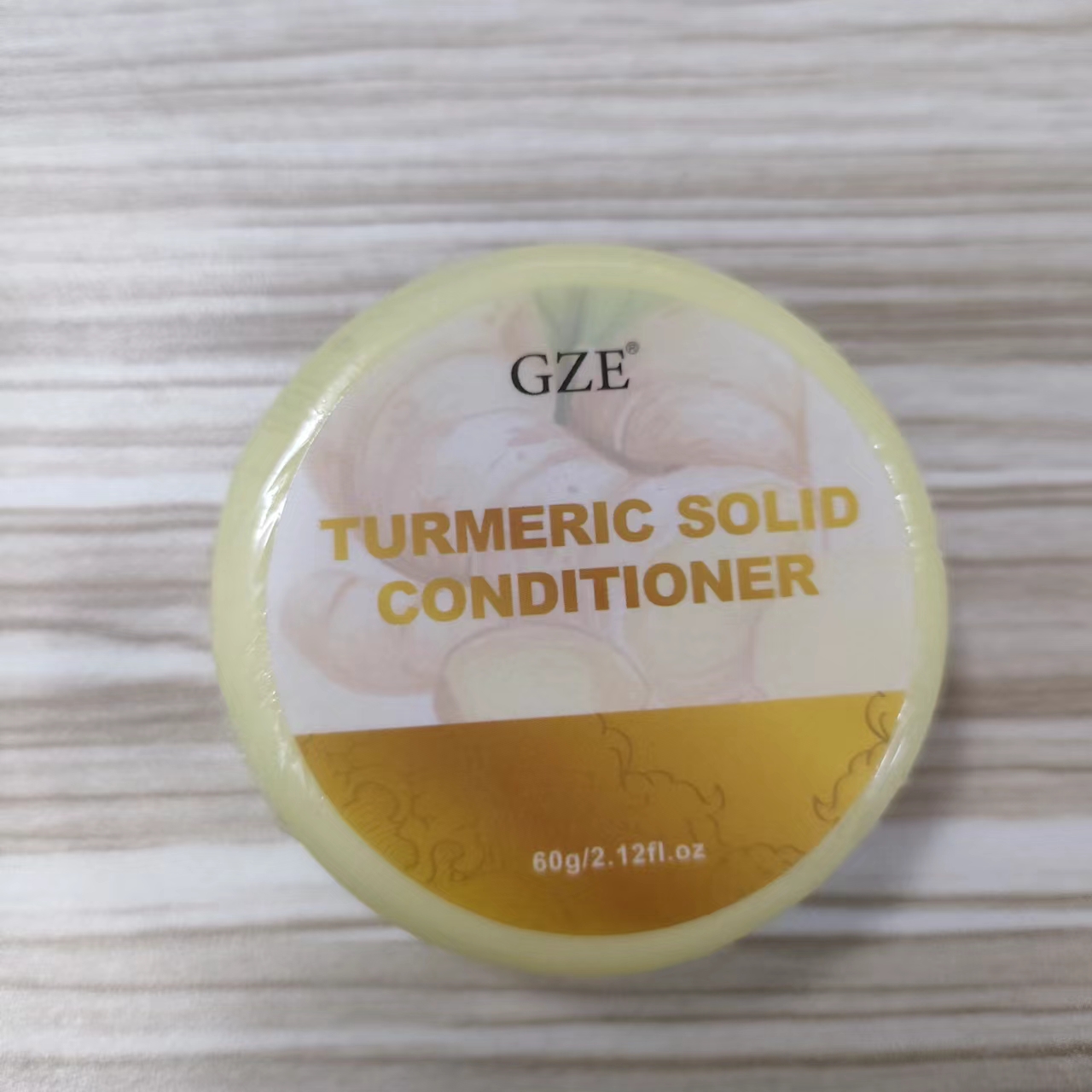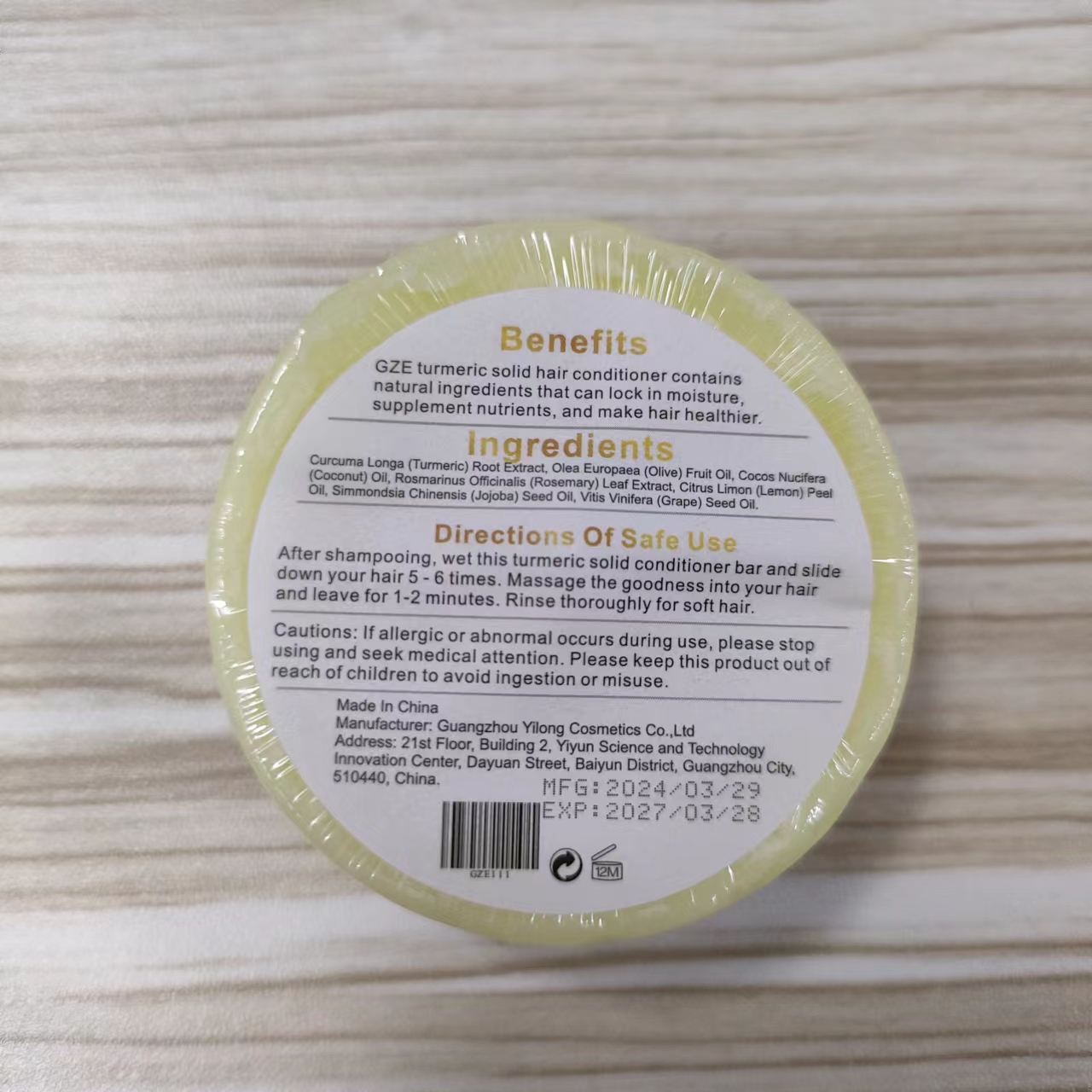 DRUG LABEL: GZE Turmeric SolidConditioner
NDC: 83566-011 | Form: SOAP
Manufacturer: Guangzhou Yilong Cosmetics Co.,Ltd.
Category: otc | Type: HUMAN OTC DRUG LABEL
Date: 20240703

ACTIVE INGREDIENTS: CURCUMA LONGA WHOLE 35 g/100 g
INACTIVE INGREDIENTS: ROSMARINUS OFFICINALIS WHOLE; OLEA EUROPAEA FRUIT VOLATILE OIL; COCONUT OIL; SIMMONDSIA CHINENSIS SEED; CITRUS LIMON FRUIT OIL; VITIS VINIFERA SEED

GZE Turmeric SolidConditioner

ACTIVE INGREDIENT

CURCUMA LONGA

INACTIVE INGREDIENT

ROSMARINUS OFFICINALIS WHOLE
OLEA EUROPAEA FRUIT VOLATILE OIL
COCONUT OIL
SIMMONDSIA CHINENSIS SEED
CITRUS LIMON FRUIT OIL
VITIS VINIFERA SEED

PURPOSE

GZE turmeric solid hair conditioner contains natural ingredients that can lock in moisture supplement nutrients, and make hair healthier.

INDICATIONS AND USAGE

After shampooing, wet this turmeric solid conditioner bar and slide down yourhair 5-6 times.Massage the goodness into your hair and leave for 1-2 minutes.Rinse thoroughly for soft hair.

WARNINGS

For external use only.

Stop use and ask a doctor if rash occurs.

Do not use on damaged or broken skin.

When using this product keep out of eyes. Rinse with water to remove.

Keep out of reach of children. If swallowed, get medical help or contact a Poison Control Center right away.

DOSAGE AND ADMINISTRATION

After shampooing, wet this turmeric solid conditioner bar and slide down your hair 5-6 times.Massage the goodness into your hair and leave for 1-2 minutes.Rinse thoroughly for soft hair.